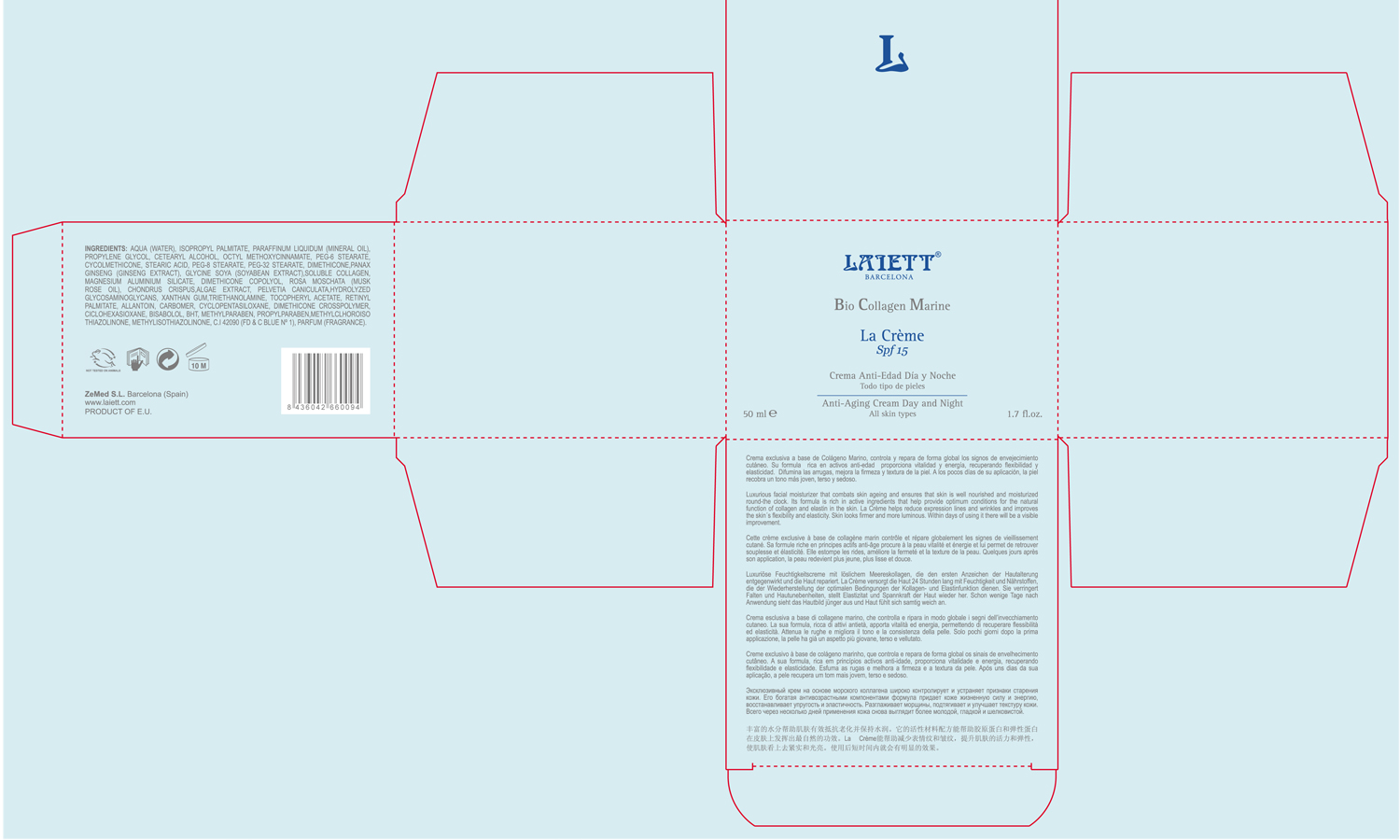 DRUG LABEL: La Creme Plus
NDC: 42248-111 | Form: CREAM
Manufacturer: Zenith Medicosm SL
Category: otc | Type: HUMAN OTC DRUG LABEL
Date: 20120213

ACTIVE INGREDIENTS: OCTINOXATE 3.75 mL/50 mL
INACTIVE INGREDIENTS: MAGNESIUM ALUMINUM SILICATE; PROPYLPARABEN; ALPHA-TOCOPHEROL ACETATE; DIMETHICONE; XANTHAN GUM; MINERAL OIL; WATER; ISOPROPYL PALMITATE; PEG-6 STEARATE; PEG-8 STEARATE; CYCLOMETHICONE; ASIAN GINSENG; CHONDRUS CRISPUS; BUTYLATED HYDROXYTOLUENE; ROSA MOSCHATA OIL ; CARBOMER 934; SOYBEAN GERM; PELVETIA CANALICULATA; METHYLPARABEN; COLLAGEN, SOLUBLE, FISH SKIN; PEG-32 STEARATE; TROLAMINE; HYDROLYZED GLYCOSAMINOGLYCANS (BOVINE; 50000 MW); STEARIC ACID; LEVOMENOL; ALLANTOIN; METHYLCHLOROISOTHIAZOLINONE; VITAMIN A PALMITATE; PROPYLENE GLYCOL; METHYLISOTHIAZOLINONE; CYCLOMETHICONE 5; CYCLOMETHICONE 6; FD&C BLUE NO. 1

Drug Facts

Active Ingredient

Octinoxate 7.5%

Description

Luxurious facial moisturizer that combats skin ageing and ensures that skin is well nourished and moisturized round-the clock. Its formula is rich in active ingredients that help provide optimum conditions for the natural function of collagen and elastin in the skin. La Creme helps reduce expression lines and wrinkles and improves the skin's flexibility and elasticity. Skin looks firmer and more luminous. Within days of using it there will be a visible improvement.

50ml. 1.7fl. oz.